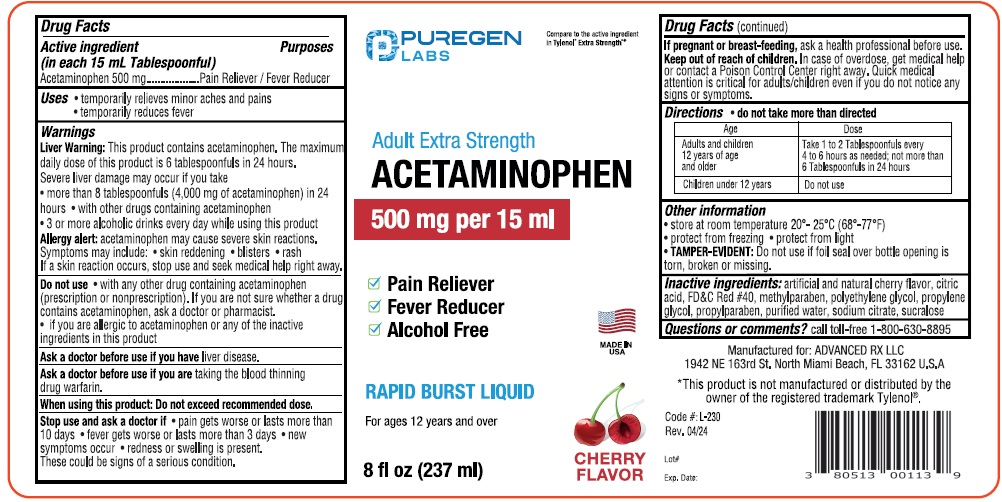 DRUG LABEL: Puregen Labs Acetaminophen
NDC: 80513-001 | Form: LIQUID
Manufacturer: Advanced Rx LLC
Category: otc | Type: HUMAN OTC DRUG LABEL
Date: 20251231

ACTIVE INGREDIENTS: ACETAMINOPHEN 500 mg/15 mL
INACTIVE INGREDIENTS: SODIUM CITRATE; METHYLPARABEN; FD&C RED NO. 40; PROPYLPARABEN; CITRIC ACID; WATER; SUCRALOSE; PROPYLENE GLYCOL; POLYETHYLENE GLYCOL, UNSPECIFIED

Puregen APAP 001

ACTIVE INGREDIENT

Acetaminophen 500 mg

PURPOSE

Pain Relever/Fever Reducer

USES

- temporarily relieves minor aches and pains due to
- headache
- toothache
- muscular aches
- the common cold
- backache
- minor pain from arthritis
- premenstrual and menstrual cramps
- temporarily reduces fever

Warnings

Liver Warning: This product contains acetaminophen. The maxium daily dose of this product is 90 mL in 24 hours. Severe liver damage may occur if you take

- more than 120 ml (4,000 mg of acetaminophen) in 24 hours
- with other drusg containing acetaminophen
- 3 or more alcoholic drinks every day while using this product

Allergy Alert: Acetaminophen may cause skin reactions. Symptoms may include:

- skin reddening
- blisters
- rash
- if a skin reaction occurs, stop use and seek medical help right away.

Do not use

- with any other drug containing acetaminophen (prescription or nonprescription). If you are not sure whether a drug contains acetaminophen, ask a doctor or pharmacist
- if you are allergic to acetaminophen or any of the inactive ingredients in this product

Ask a doctor before use if you have liver disease.

Ask a doctor before use if you are taking the blood thinning drug warafin

When using this product: Do not exceed recommeneded dose.

Stop use and ask a doctor if

- pain gets worse or lasts more than 10 days
- fever get worse or lasts more than 3 days
- new symptoms occur
- redness or swelling is present. These could be signs of a serious condition.

PREGNANCY OR BREAST FEEDING

If pregnant or breast-feeding, ask a health professional before use

Keep out of reach of children. In case of overdose, get medical help or contact a Poison Control Center (1-800-222-1222) right away.

Directions

- do not take more than directed

Age | Dose
Adults and children 12 years of age and older | Take 1 to 2 tablespoonfuls every 4 to 6 hours as needed. Not more than 6 tablespoonfuls in 24 hours
Children under 12 years | do not use

INACTIVE INGREDIENT

Inactive ingredients: artificail and natural cherry flavor, citric acid, FD&C Red #40, methylparaben, polyethylene glycol, propylene glycol, propylparaben, purified water, sodium citrate, sucralose

Questions or comments? 1-800-630-8895

RECENT MAJOR CHANGES

Fix typos